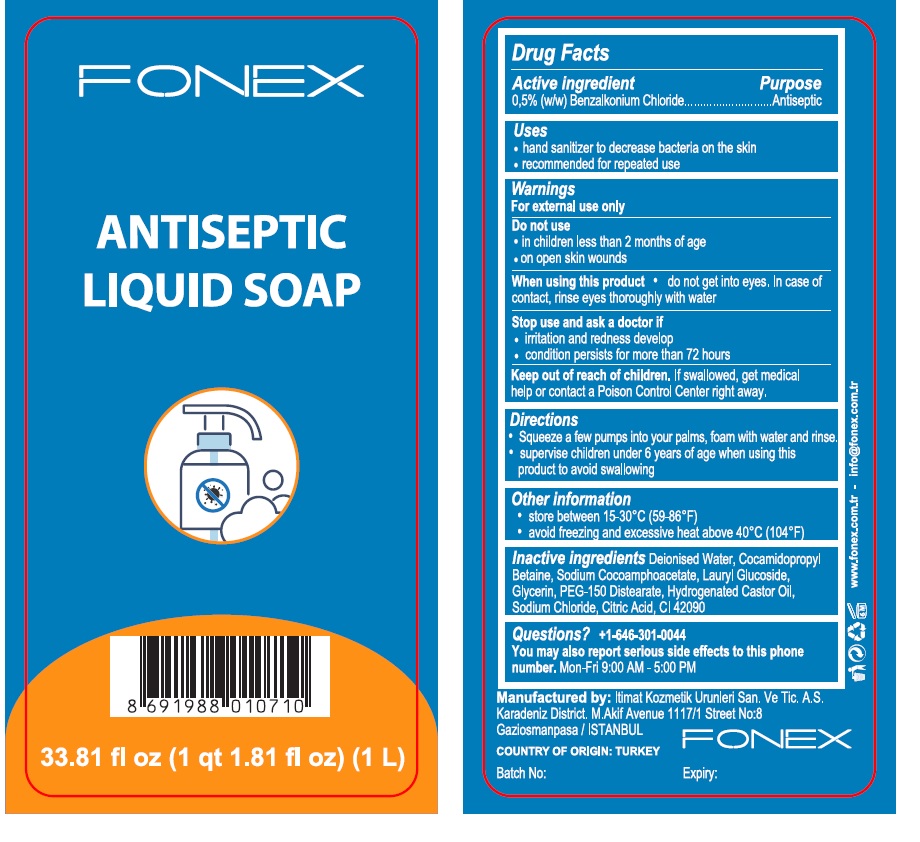 DRUG LABEL: Antiseptic Liquid
NDC: 79392-102 | Form: SOAP
Manufacturer: ITIMAT KOZMETIK URUNLERI SANAYI VE TICARET ANONIM SIRKETI
Category: otc | Type: HUMAN OTC DRUG LABEL
Date: 20200720

ACTIVE INGREDIENTS: BENZALKONIUM CHLORIDE 0.5 g/100 mL
INACTIVE INGREDIENTS: WATER; COCAMIDOPROPYL BETAINE; SODIUM COCOAMPHOACETATE; LAURYL GLUCOSIDE; GLYCERIN; PEG-150 DISTEARATE; HYDROGENATED CASTOR OIL; SODIUM CHLORIDE; CITRIC ACID MONOHYDRATE; FD&C BLUE NO. 1

FONEX ANTISEPTIC LIQUID SOAP

Active ingredient

0,5% (w/w) Benzalkonium Chloride

Purpose

Antiseptic

Uses

• hand sanitizer to decrease bacteria on the skin
• recommended for repeated use

Warnings

For external use only

Do not use

• in children less than 2 months of age
• on open skin wounds

When using this product • do not get into eyes. In case of contact, rinse eyes thoroughly with water
Stop use and ask a doctor if
• irritation and redness develop
• condition persists for more than 72 hours

Keep out of reach of children.

If swallowed, get medical help or contact a Poison Control Center right away.

Directions

• Squeeze a few pumps into your palms, foam with water and rinse.
• supervise children under 6 years of age when using this product to avoid swallowing

Other information

• store between 15-30°C (59-86°F)
• avoid freezing and excessive heat above 40°C (104°F)

Inactive ingredients

Deionised Water, Cocamidopropyl Betaine, Sodium Cocoamphoacetate, Lauryl Glucoside, Glycerin, PEG-150 Distearate, Hydrogenated Castor Oil,
Sodium Chloride, Citric Acid, CI 42090

Questions?

+1-646-301-0044
You may also report serious side effects to this phone number.

Mon-Fri 9:00 AM - 5:00 PM

Manufactured by: Itimat Kozmetik Urunleri San. Ve Tic. A.S.
Karadeniz District. M.Akif Avenue 1117/1 Street No:8
Gaziosmanpasa / ISTANBUL
COUNTRY OF ORIGIN: TURKEY
Batch No:

Expiry:

www.fonex.com.tr - info@fonex.com.tr